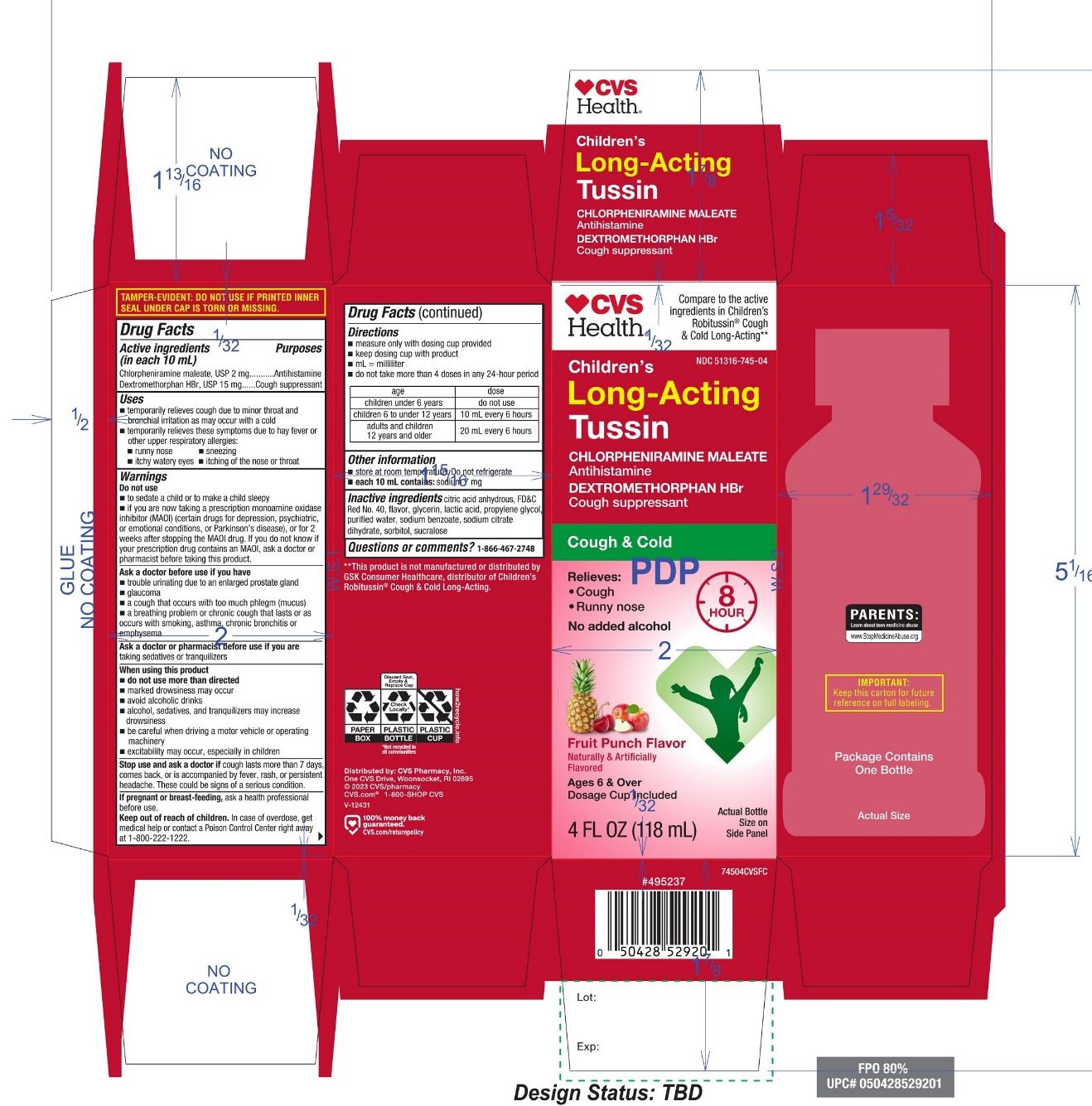 DRUG LABEL: CVS childrens Cough and Cold
NDC: 51316-745 | Form: LIQUID
Manufacturer: CVS PHARMACY
Category: otc | Type: HUMAN OTC DRUG LABEL
Date: 20251210

ACTIVE INGREDIENTS: CHLORPHENIRAMINE MALEATE 2 mg/10 mL; DEXTROMETHORPHAN HYDROBROMIDE 15 mg/10 mL
INACTIVE INGREDIENTS: ANHYDROUS CITRIC ACID; FD&C RED NO. 40; GLYCERIN; LACTIC ACID, UNSPECIFIED FORM; PROPYLENE GLYCOL; WATER; SODIUM BENZOATE; SODIUM CITRATE, UNSPECIFIED FORM; SORBITOL; SUCRALOSE

CVS Children’s Cough & Cold Drug Facts

ACTIVE INGREDIENTS (in each 10 mL)

Chlorpheniramine maleate, USP 2 mg

Dextromethorphan HBr, USP 15 mg

PURPOSES

Antihistamine

Cough suppressant

Uses

- temporarily relieves cough due to minor throat and bronchial irritation as may occur with a cold
- temporarily relieves these symptoms due to hay fever or other upper respiratory allergies:
  - runny nose
  - sneezing
  - itchy, watery eyes
  - itching of the nose or throat

WARNINGS

Do not use

- to sedate a child or to make a child sleepy
- if you are now taking a prescription monoamine oxidase inhibitor (MAOI) (certain drugs for depression, psychiatric, or emotional conditions, or Parkinson's disease), or for 2 weeks after stopping the MAOI drug. If you do not know if your prescription drug contains an MAOI, ask a doctor or pharmacist before taking this product.

Ask a doctor before use if you have

- trouble urinating due to an enlarged prostate gland
- glaucoma
- a cough that occurs with too much phlegm (mucus)
- a breathing problem or chronic cough that lasts or as occurs with smoking, asthma, chronic bronchitis or emphysema

Ask a doctor or pharmacist before use if you are

taking sedatives or tranquilizers

When using this product

- do not use more than directed
- marked drowsiness may occur
- avoid alcoholic drinks
- alcohol, sedatives, and tranquilizers may increase drowsiness
- be careful when driving a motor vehicle or operating machinery
- excitability may occur, especially in children

Stop use and ask a doctor if

cough lasts more than 7 days, comes back, or is accompanied by fever, rash, or persistent headache. These could be signs of a serious condition.

If pregnant or breast-feeding,

ask a health professional before use.

Keep out of reach of children.

In case of overdose, get medical help or contact a Poison Control Center right away at 1-800-222-1222.

Directions

- measure only with dosing cup provided
- keep dosing cup with product
- mL = milliliter
- do not take more than 4 doses in any 24-hour period

age | dose
Children under 6 years | do not use
children 6 to under 12 years | 10 mL every 6 hours
adults and children 12 years and older | 20 mL every 6 hours

Other information

- each 10 mL contains: sodium 7 mg
- store at room temperature, Do not refrigerate.

Inactive ingredients

citric acid, FD&C red no. 40, Glycerin, lactic acid, natural and artificial flavors, propylene glycol, purified water, sodium benzoate, sodium citrate, sorbitol solution, sucralose

QUESTIONS OR COMMENTS?

1-866-467-2748

PRODUCT PACKAGING

Compare to the active ingredients in Children’s Robitussin®Cough & Cold Long–Acting*

NDC 51316-745-04

Children’s COUGH & COLD

Chlorpheniramine Maleate USP 2 mg (Antihistamine)

Dextromethorphan HBr, USP 15 mg (Cough Suppressant)

Long-Acting

Relieves:

- Cough up to 8 hours
- Runny nose
- For Ages 6 & Over

Fruit Punch Flavor

Naturally and Artificially Flavored

4 FL OZ (118 mL)

IMPORTANT: Keep this carton for future reference on full labeling

Distributed by: